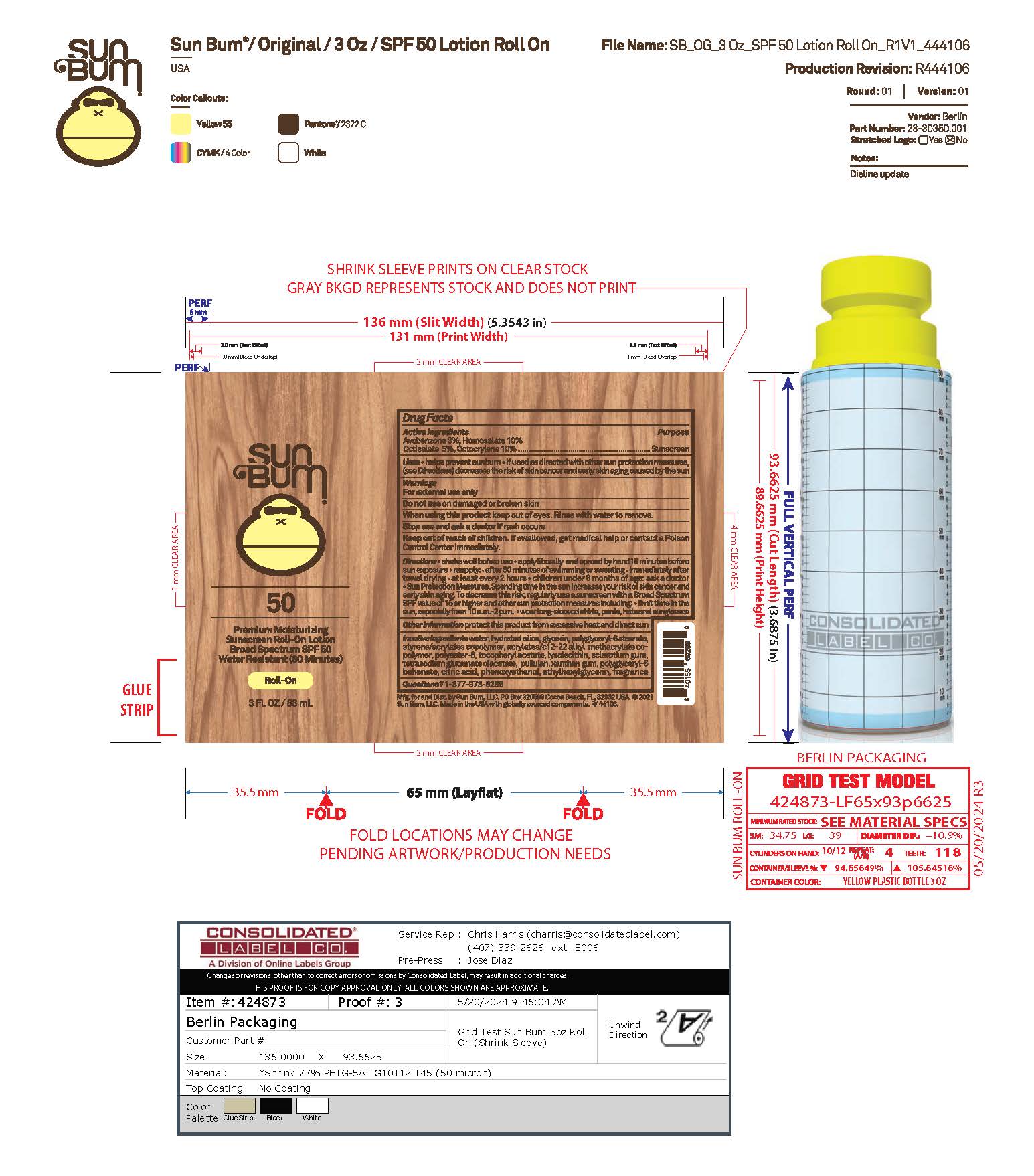 DRUG LABEL: Sun Bum 50 Premium Moisturizing Sunscreen Roll-On
NDC: 69039-800 | Form: LOTION
Manufacturer: Sun Bum, LLC
Category: otc | Type: HUMAN OTC DRUG LABEL
Date: 20250814

ACTIVE INGREDIENTS: HOMOSALATE 100 mg/1 mL; OCTISALATE 50 mg/1 mL; OCTOCRYLENE 100 mg/1 mL; AVOBENZONE 30 mg/1 mL
INACTIVE INGREDIENTS: TETRASODIUM GLUTAMATE DIACETATE; WATER; XANTHAN GUM; .ALPHA.-TOCOPHEROL ACETATE; ETHYLHEXYLGLYCERIN; GLYCERIN; PHENOXYETHANOL; PULLULAN; CITRIC ACID; POLYGLYCERYL-6 BEHENATE; ACRYLATES/C10-30 ALKYL ACRYLATE CROSSPOLYMER (60000 MPA.S); LUVISET 360; HYDRATED SILICA; POLYGLYCERYL-6 STEARATE; POLYESTER-8 (1400 MW, CYANODIPHENYLPROPENOYL CAPPED); LYSOPHOSPHATIDYLCHOLINE, SOYBEAN; SCLEROTIUM GUM

Sun Bum 50 Premium Moisturizing Sunscreen Roll-On

Active Ingredients

AVOBENZONE 3%, HOMOSALATE 10%, OCTISALATE 5%, OCTOCRYLENE 10%

Purpose

Sunscreen

Uses

• helps prevent sunburn • if used as directed with other sun protection measures, (see Directions) decreases the risk of skin cancer and early skin aging caused by the sun

Warnings

For external use only

Do not use on damaged or broken skin

When using this product keep out of eyes. Rinse with water to remove.

Stop use and ask a doctor if rash occurs

Keep out of reach of children. If swallowed, get medical help or contact a Poison Control Center immediately.

Warnings

Keep Out Of Reach Of Children

Directions

• shake well before use

• apply liberally 15 minutes before sun exposure

• reapply: • after 80 minutes of swimming or sweating • immediately after towel drying • at least every 2 hours

• children under 6 months of age: ask a doctor

• Sun Protection Measures. Spending time in the sun increases your risk of skin cancer and early skin aging. To decrease this risk, regularly use a sunscreen with a Broad Spectrum SPF value of 15 or higher and other sun protection measures including:

• limit time in the sun, especially from 10 a.m.- 2 p.m.

• wear long-sleeved shirts, pants, hats and sunglasses

Directions

• shake well before use

• apply liberally 15 minutes before sun exposure

Other Information

protect this product from excessive heat and direct sun

Inactive Ingredients

water, hydrated silica, glycerin, polyglyceryl-6 stearate, styrene/acrylates copolymer, acrylates/c12-22 alkyl methacrylate copolymer, polyester-8, tocopheryl acetate, lysolecithin, sclerotium gum, tetrasodium glutamate diacetate, pullulan, xanthan gum, polyglyceryl-6 behenate, citric acid, phenoxyethanol, ethylhexylglycerin, fragrance

Questions?

1-877-978-6286